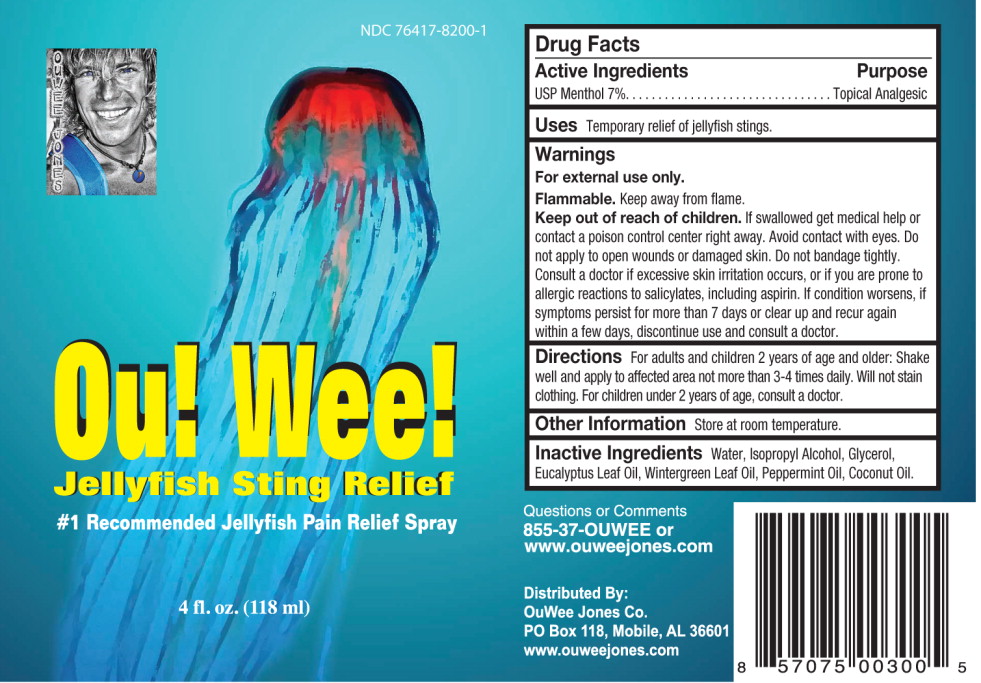 DRUG LABEL: Analgesic
NDC: 76417-8200 | Form: SPRAY
Manufacturer: Ouwee Jones, LLC
Category: otc | Type: HUMAN OTC DRUG LABEL
Date: 20111026

ACTIVE INGREDIENTS: menthol 700 mL/1 L
INACTIVE INGREDIENTS: water; isopropyl alcohol; glycerin; eucalyptus oil; methyl salicylate; peppermint oil; coconut oil

OuWee Jones PAIN RELIEF SPRAY

Pain Spray

Drug Facts

Active Ingredients

USP Menthol 7%

Purpose

Topical Analgesic

Uses

Temporary relief of jellyfish stings.

Warnings

For external use only

Flammable. Keep away from flame.

Keep out of reach of children. If swallowed get medical help or contact a poison center right away. Avoid contact with eyes. Do not apply to open wounds or damaged skin. Do not bandage tightly. Consult a doctor if excessive skin irritation occurs, or if you are prone to allergic reactions to salicylates, including aspirin. If condition worsens, if symptoms persist for more than 7 days or clear up and recur again within a few days, discontinue use of this product and consult a doctor.

Directions

For adults and children 2 years of age and older: Shake well and apply to affected area not more than 3-4 times daily. Will not stain clothing. For children under 2 years of age, consult a doctor.

Other Information

Store at room temperature.

Inactive Ingredients

Water, Isopropyl Alcohol, Glycerol, Eucalyptus Leaf Oil, Wintergreen Leaf Oil, Peppermint Oil, Coconut Oil.

Questions or Comments
855-37-OUWEE or
www.ouweejones.com

Distributed By:
OuWee Jones Co.
PO Box 118, Mobile, AL 36601
www.ouweejones.com

PRINCIPAL DISPLAY PANEL

NDC 76417-8200-1

Ou! Wee!

Jellyfish Sting Relief

#1 Recommended Jellyfish Pain Relief Spray

4 fl. oz. (118 ml)